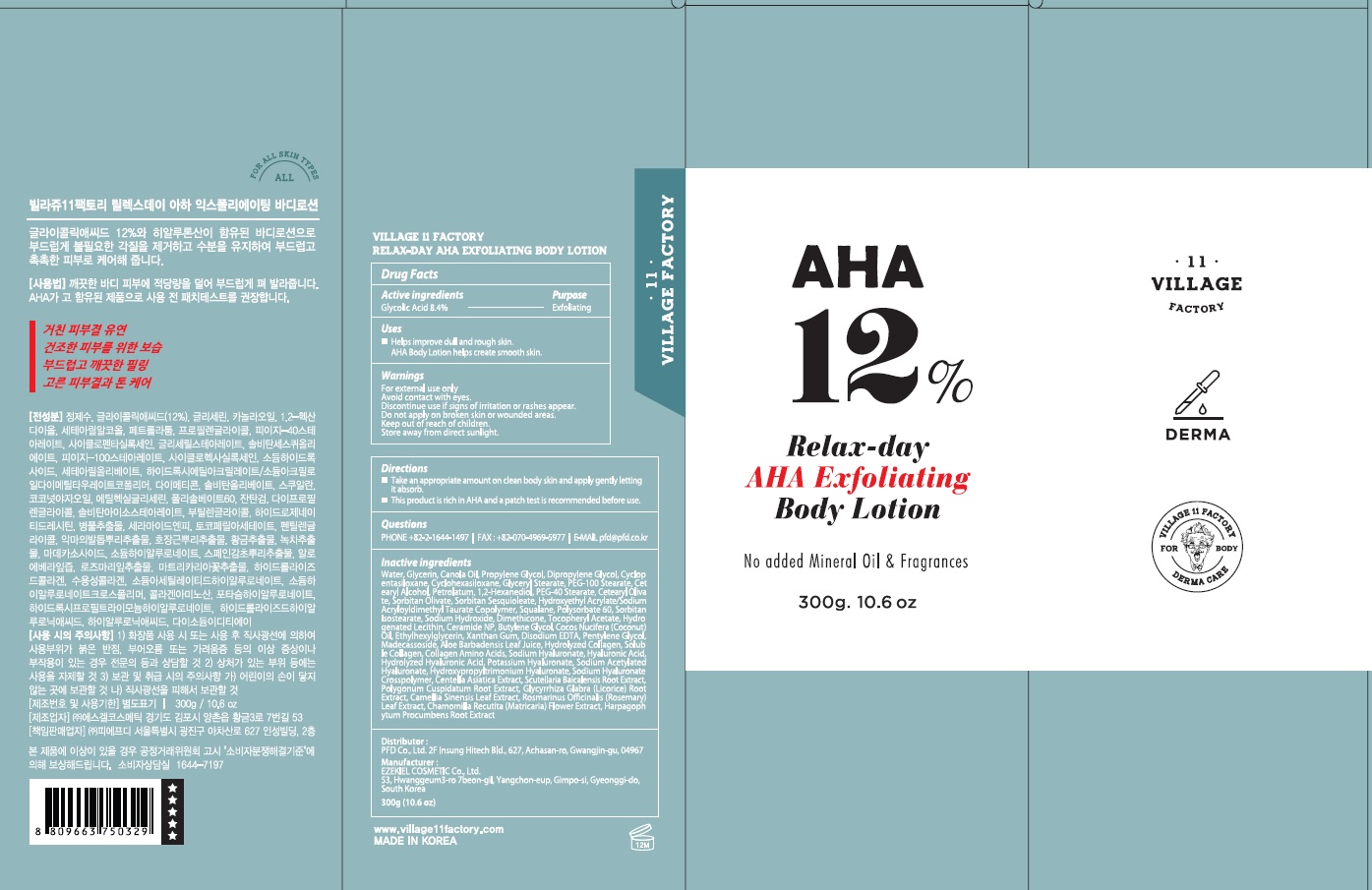 DRUG LABEL: VILLAGE 11 FACTORY RELAX DAY AHA EXFOLIATING BODY
NDC: 72470-050 | Form: LOTION
Manufacturer: PFD Co.,Ltd.
Category: otc | Type: HUMAN OTC DRUG LABEL
Date: 20201201

ACTIVE INGREDIENTS: Glycolic Acid 25.2 g/300 g
INACTIVE INGREDIENTS: Water; Glycerin; CANOLA OIL

ACTIVE INGREDIENT

Glycolic Acid 8.4%

INACTIVE INGREDIENTS

Water, Glycerin, Canola Oil, Propylene Glycol, Dipropylene Glycol, Cyclopentasiloxane, Cyclohexasiloxane, Glyceryl Stearate, PEG-100 Stearate, Cetearyl Alcohol, Petrolatum, 1,2-Hexanediol, PEG-40 Stearate, Cetearyl Olivate, Sorbitan Olivate, Sorbitan Sesquioleate, Hydroxyethyl Acrylate/Sodium Acryloyldimethyl Taurate Copolymer, Squalane, Polysorbate 60, Sorbitan Isostearate, Sodium Hydroxide, Dimethicone, Tocopheryl Acetate, Hydrogenated Lecithin, Ceramide NP, Butylene Glycol, Cocos Nucifera (Coconut) Oil, Ethylhexylglycerin, Xanthan Gum, Disodium EDTA, Pentylene Glycol, Madecassoside, Aloe Barbadensis Leaf Juice, Hydrolyzed Collagen, Soluble Collagen, Collagen Amino Acids, Sodium Hyaluronate, Hyaluronic Acid, Hydrolyzed Hyaluronic Acid, Potassium Hyaluronate, Sodium Acetylated Hyaluronate, Hydroxypropyltrimonium Hyaluronate, Sodium Hyaluronate Crosspolymer, Centella Asiatica Extract, Scutellaria Baicalensis Root Extract, Polygonum Cuspidatum Root Extract, Glycyrrhiza Glabra (Licorice) Root Extract, Camellia Sinensis Leaf Extract, Rosmarinus Officinalis (Rosemary) Leaf Extract, Chamomilla Recutita (Matricaria) Flower Extract, Harpagophytum Procumbens Root Extract

PURPOSE

Exfoliating

WARNINGS

For external use only
Avoid contact with eyes.
Discontinue use if signs of irritation or rashes appear.
Do not apply on broken skin or wounded areas.
Keep out of reach of children
Store away from direct sunlight

KEEP OUT OF REACH OF CHILDREN

Uses

■ Helps improve dull and rough skin. AHA Body Lotion helps create smooth skin.

Directions

■ Take an appropriate amount on clean body skin and apply gently letting it absorb.
■ This product is rich in AHA and a patch test is recommended before use.

QUESTIONS

PHONE +82-2-1644-1497 | FAX : +82-070-4969-5977 | E-MAIL pfd@pfd.co.kr